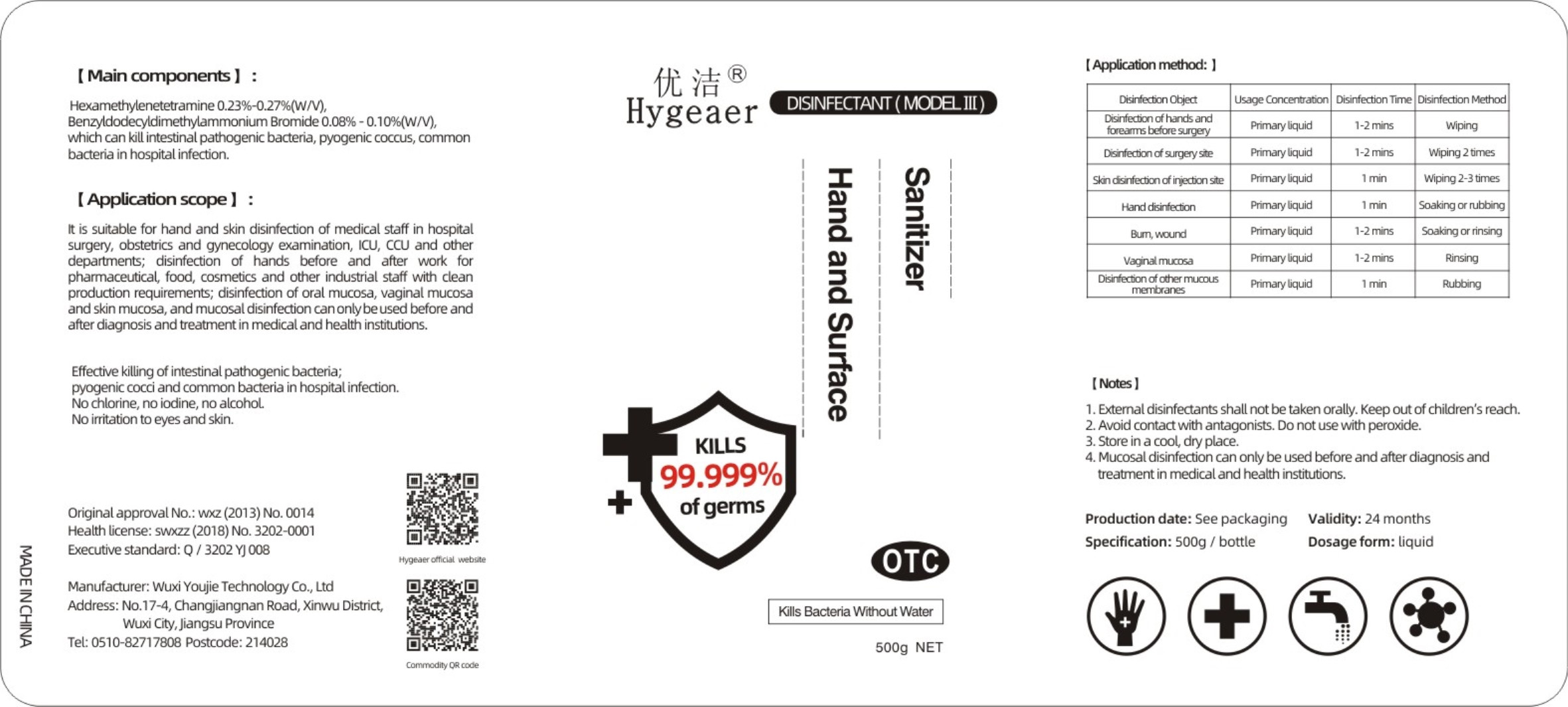 DRUG LABEL: Disinfectant(Model III)Sanitizer Hand And Surface
NDC: 54796-006 | Form: LIQUID
Manufacturer: Wuxi Youjie Technology Co. LTD
Category: otc | Type: HUMAN OTC DRUG LABEL
Date: 20200428

ACTIVE INGREDIENTS: METHENAMINE 1.25 g/500 g; BENZALKONIUM BROMIDE 0.45 g/500 g
INACTIVE INGREDIENTS: WATER

DOSAGE AND ADMINISTRATION

Don't put it in a damp place.

INACTIVE INGREDIENT

water

INDICATIONS AND USAGE

Wipe the product directly and spread for 1-2 minutes.

ACTIVE INGREDIENT

HEXAMETHYLENETETRAMINE

BENZALKONIUM BROMIDE

keep out of reach of children

PURPOSE

Disinfection
Sterilization

WARNINGS

Extemnal disinfectants shall not be taken orally. Keep out of children's reach.Avolid contact with antagonists.